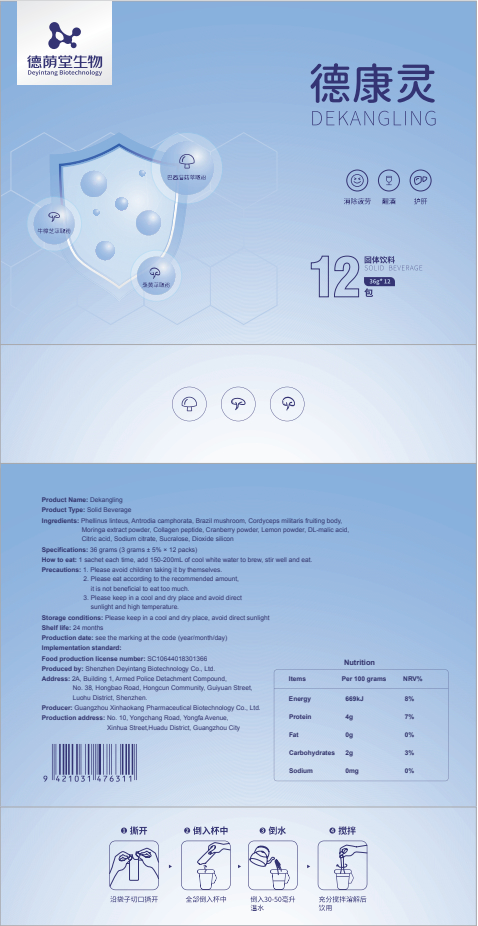 DRUG LABEL: Dekangling
NDC: 82570-010 | Form: POWDER
Manufacturer: Shenzhen Deyintang Biotechnology Co., Ltd.
Category: otc | Type: HUMAN OTC DRUG LABEL
Date: 20220221

ACTIVE INGREDIENTS: CULTIVATED MUSHROOM 7 g/100 g; CORDYCEPS MILITARIS FRUITING BODY 10 g/100 g; MORINGA OLEIFERA LEAF 7 g/100 g; COLLAGEN, SOLUBLE, FISH SKIN 20 g/100 g; POMIFERIN 7 g/100 g; TAIWANOFUNGUS CAMPHORATUS MYCELIUM 4 g/100 g
INACTIVE INGREDIENTS: LEMON; MALIC ACID; CRANBERRY; CITRIC ACID MONOHYDRATE; SODIUM CITRATE; SUCRALOSE; SILICON DIOXIDE

ACTIVE INGREDIENT

Phellinus linteus, Antrodia camphorata,Brazil mushroom, Cordyceps militaris fruiting body,Moringa extract powder, Collagen peptide

INACTIVE INGREDIENT

Cranberry powder, Lemon powder, DL-malic acid,Citric acid, Sodium citrate, Sucralose,Dioxide silicon

PURPOSE

health care

Please avoid children taking it by themselves.

How to eat

1 sachet each time, add 150-200mL of cool white water to brew, stir well and eat.

INDICATIONS AND USAGE

Please eat according to the recommended amount,it is not beneficial to eat too much.

Storage conditions

Please keep in a cool and dry place, avoid direct sunlight

WARNINGS

1.Please avoid children taking it by themselves.
2.Please eat according to the recommended amount,it is not beneficial to eat too much.
3.Please keep in a cool and dry place and avoid directsunlight and high temperature.